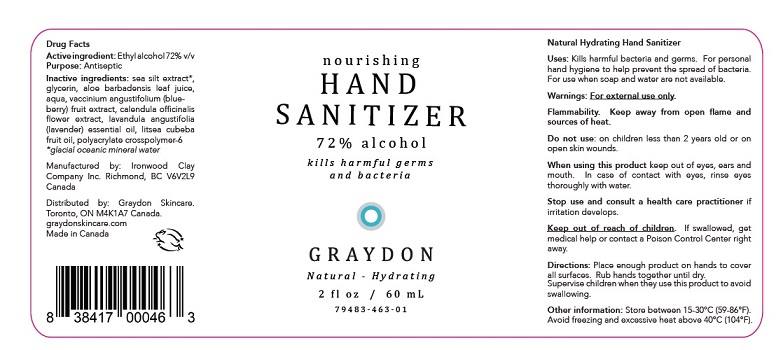 DRUG LABEL: Graydon Natural-Hydrating
NDC: 79483-463 | Form: LIQUID
Manufacturer: Graydon Skincare
Category: otc | Type: HUMAN OTC DRUG LABEL
Date: 20211206

ACTIVE INGREDIENTS: ALCOHOL 72 mL/100 mL
INACTIVE INGREDIENTS: WATER; GLYCERIN; ALOE VERA LEAF; VACCINIUM ANGUSTIFOLIUM LEAF; CALENDULA OFFICINALIS FLOWER; LAVENDER OIL; LITSEA CUBEBA FRUIT; AMMONIUM ACRYLOYLDIMETHYLTAURATE, DIMETHYLACRYLAMIDE, LAURYL METHACRYLATE AND LAURETH-4 METHACRYLATE COPOLYMER, TRIMETHYLOLPROPANE TRIACRYLATE CROSSLINKED (45000 MPA.S)

DRUG FACTS

Active ingredient: Ethyl alcohol 72% v/v

Purpose: Antiseptic

INDICATIONS AND USAGE

Uses: Kills harmful bacteria and germs. For personal
hand hygiene to help prevent the spread of bacteria.
For use when soap and water are not available.

Warnings: For external use only.
Flammability. Keep away from open flame and
sources of heat.

Do not use: on children less than 2 years old or on
open skin wounds.

When using this product keep out of eyes, ears and
mouth. In case of contact with eyes, rinse eyes
thoroughly with water.

Stop use and consult a health care practitioner if
irritation develops.

Keep out of reach of children. If swallowed, get
medical help or contact a Poison Control Center right
away.

DOSAGE AND ADMINISTRATION

Directions: Place enough product on hands to cover
all surfaces. Rub hands together until dry.
Supervise children when they use this product to avoid
swallowing.

OTHER INFORNMATION
·Store between 15-30C (59-86F)
·Avoid freezing and excessive heat above 40C (104F)

Inactive ingredients: sea silt extract*,
glycerin, aloe barbadensis leaf juice,
aqua, vaccinium angustifolium (blueberry)
fruit extract, calendula officinalis
flower extract, lavandula angustifolia
(lavender) essential oil, litsea cubeba
fruit oil, polyacrylate crosspolymer-6
*glacial oceanic mineral water

Package Labeling

n o u r i s h i n g

HAND

SANITIZER

72% alcohol

k i l l s h a r m f u l g e r m s
a n d b a c t e r i a

GRAYDON

N a t u r a l - H y d r a t i n g

2 fl oz / 60 mL

7 4 9 8 3 - 4 6 3 - 0 1

Manufactured by: Ironwood Clay
Company Inc. Richmond, BC V6V2L9
Canada

Distributed by: Graydon Skincare.
Toronto, ON M4K1A7 Canada.
graydonskincare.com
Made in Canada

res